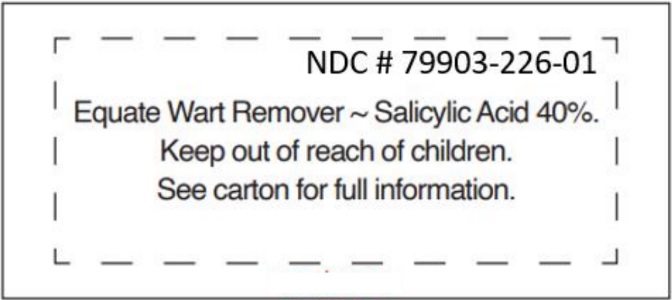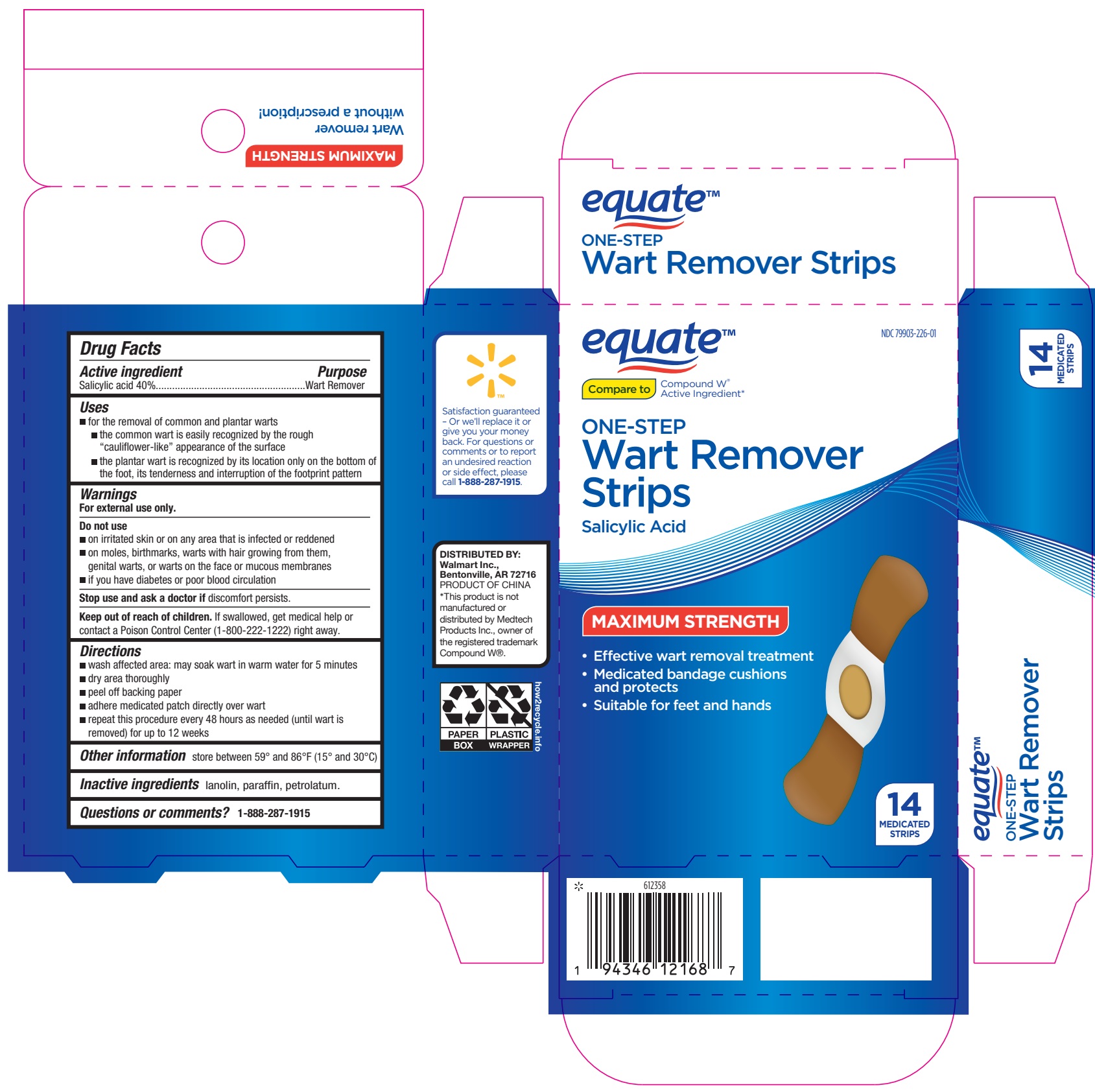 DRUG LABEL: Equate One Step Wart Remover Strips
NDC: 79903-226 | Form: PLASTER
Manufacturer: Walmart Inc.
Category: otc | Type: HUMAN OTC DRUG LABEL
Date: 20250104

ACTIVE INGREDIENTS: SALICYLIC ACID 40 mg/1 1
INACTIVE INGREDIENTS: LANOLIN; PARAFFIN; PETROLATUM

Equate One Step Wart Remover Strips

Active ingredient

Salicylic acid 40%

Purpose

Wart Remover

Uses

- for the removal of common and plantar warts
- the common wart is easily recognized by the rough “cauliflower-like” appearance of the surface
- the plantar wart is recognized by its location only on the bottom of the foot, its tenderness and interruption of the footprint pattern

Warnings

For external use only.

Do not use

- on irritated skin or on any area that is infected or reddened
- on moles, birthmarks, warts with hair growing from them, genital warts, or warts on the face or mucous membranes
- if you have diabetes or poor blood circulation

Stop use and ask a doctor if

discomfort persists.

Keep out of reach of children.

If swallowed, get medical help or contact a Poison Control Center (1-800-222-1222) right away.

Directions

- wash affected area: may soak wart in warm water for 5 minutes
- dry area thoroughly
- peel off backing paper
- adhere medicated patch directly over wart
- repeat this procedure every 48 hours as needed (until wart is removed) for up to 12 weeks

Other information

store between 59° and 86°F (15° and 30°C)

Inactive ingredients

lanolin, paraffin, petrolatum.

Questions or comments?

1-888-287-1915